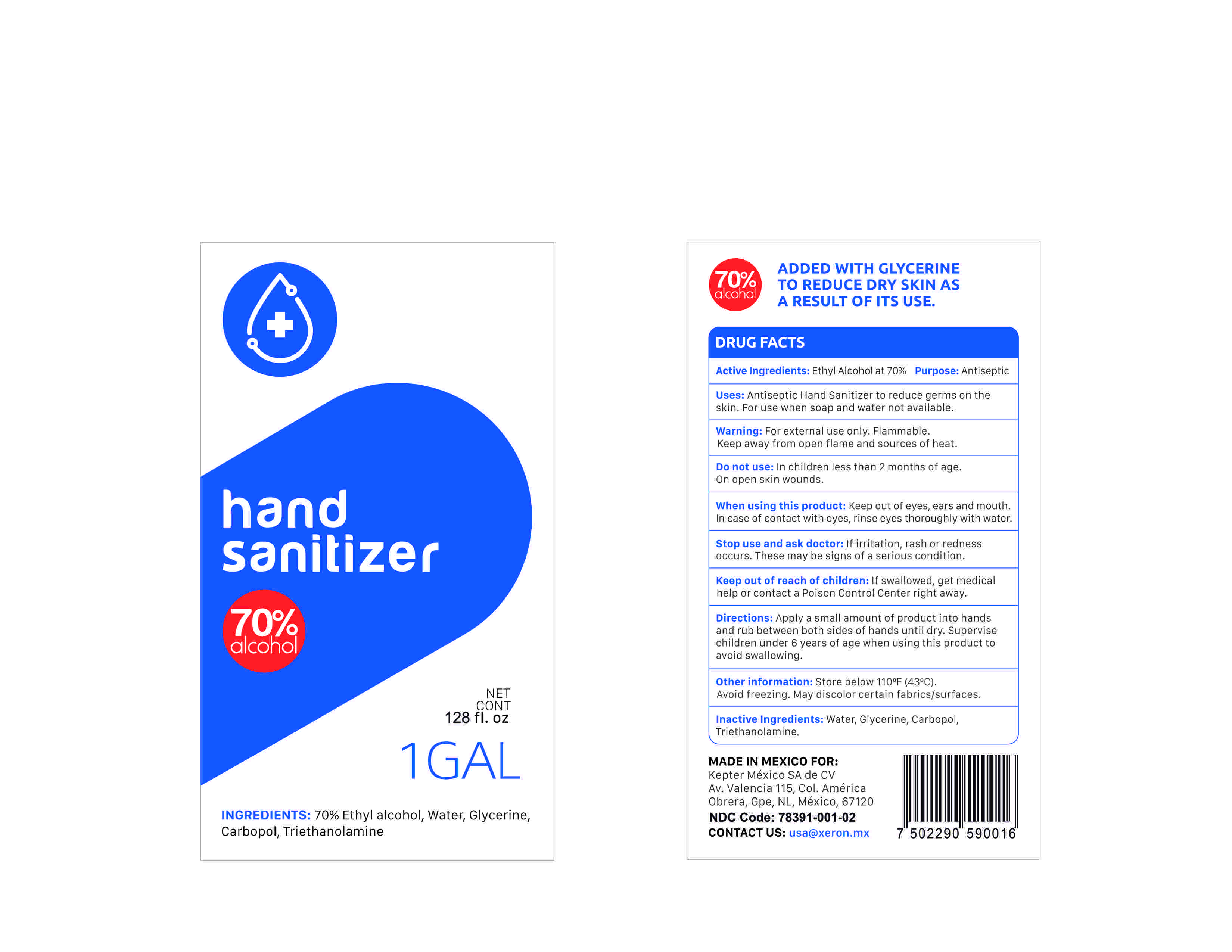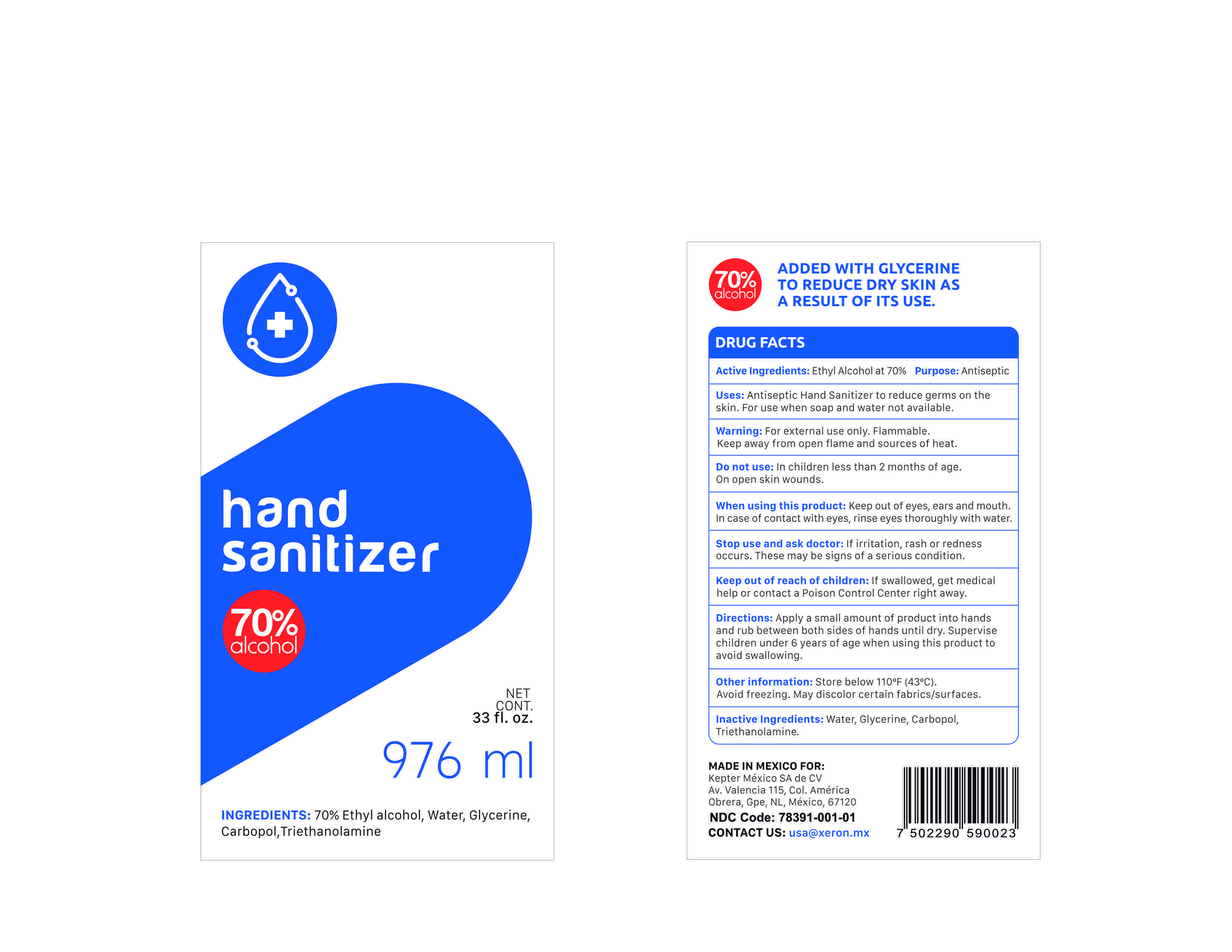 DRUG LABEL: Hand Sanitizer
NDC: 78391-001 | Form: GEL
Manufacturer: Kepter Mexico S.A de C.V
Category: otc | Type: HUMAN OTC DRUG LABEL
Date: 20200623

ACTIVE INGREDIENTS: ALCOHOL 70 mL/100 mL
INACTIVE INGREDIENTS: WATER 28 mL/100 mL; GLYCERIN 0.5 mL/100 mL; TROLAMINE 0.4 mL/100 mL; CARBOMER 940 0.5 mL/100 mL

Hand Sanitizer

This is a hand sanitizer manufactured using only the following United States Pharmacopoeia (USP) grade ingredients:

a. Alcohol (ethanol) (USP of Food Chemical Codex (FCC) grade) (70%, volume/volume (v/v) in an aqueous solution denatured according to Alcohol and Tobacco Tax and Trade Bureau regulations in 27 CFR part 20.

b. Glycerin (.5% v/v).

c. Carbopol (.5% v/v).

d. Triethanolamine (.4% v/v).

e. Sterile distilled water or boiled cold water.

Active Ingredient(s)

Ethyl Alcohol 70% v/v. Purpose: Antiseptic

Purpose

Antiseptic, Hand Sanitizer

Use

Antiseptic Hand Sanitizer to reduce germs on the skin. For use when soap and water not available.

Warnings

For external use only. Flammable. Keep away from open flame and sources of heat.

Do not use

in children less than 2 months of age. On open skin wounds.

When using this product: Keep out of eyes, ears and mouth. In case of contact with eyes, rinse eyes thoroughly with water.

Stop use and ask doctor: If irritation, rash or redness ocurrs. These may be signs of a serious condition.

Keep out reach of children: If swallowed, get medical help or contat a Posion Control Center right away.

Stop use and ask doctor: If irritation, rash or redness occurs. These may be signs of a serious condition.

Keep out of reach of children. If swallowed, get medical help or contact a Posion Control Center right away.

Directions

Apply a small amount of product into hands and rub between both sides of hands until dry. Supervise children under 6 years of age when using this product to avoid swallowing.

Other information

Store below 110F (43C)

Avoid freezing. May discolor certain fabrics/surfaces.

Inactive Ingredients

Water, Glycerin, Carbopol, Triethanolamine

Package Label - Principal Display Panel

976 ml NDC: 78391-001-01

3786 ml NDC: 78391-001-02